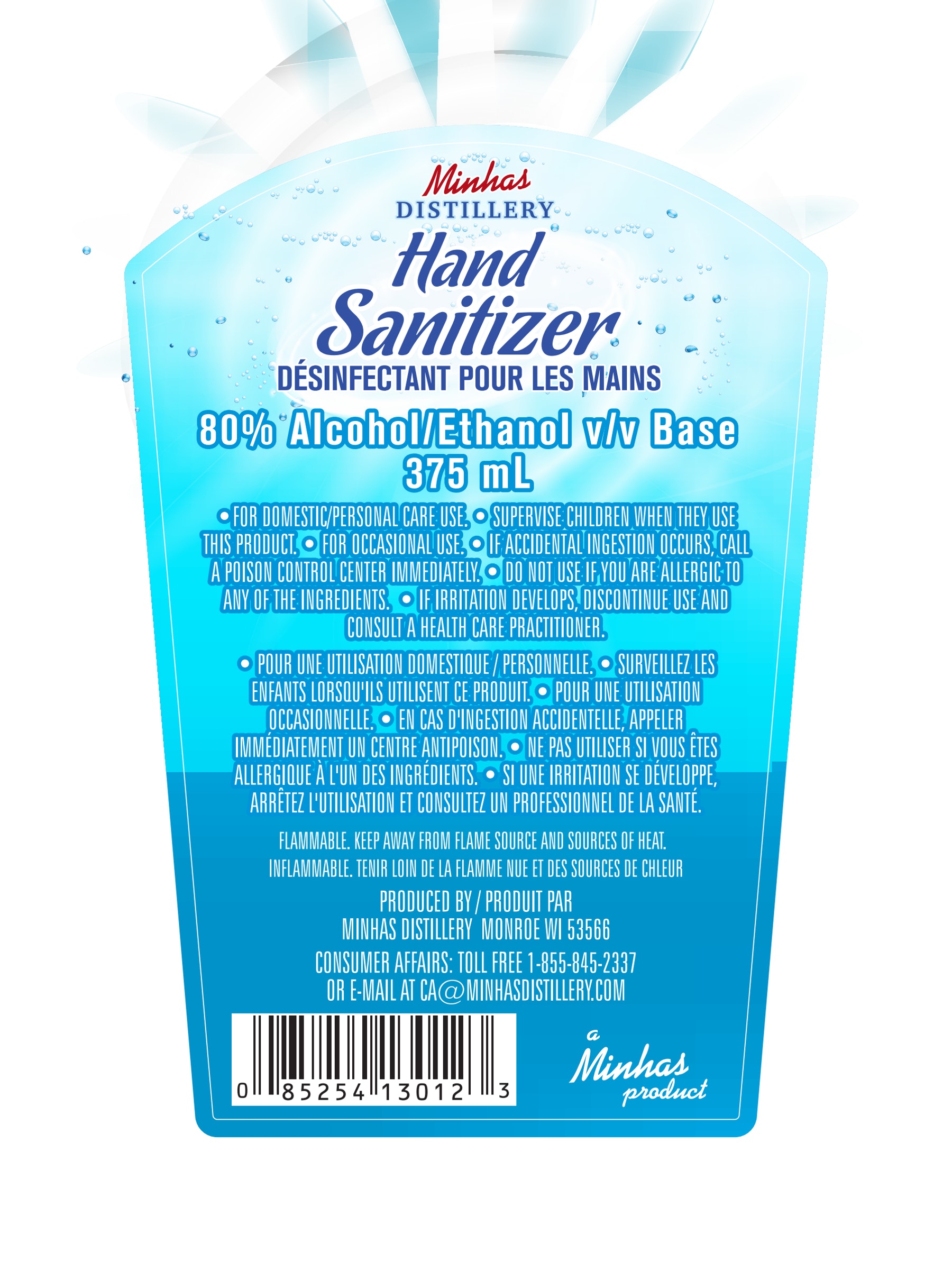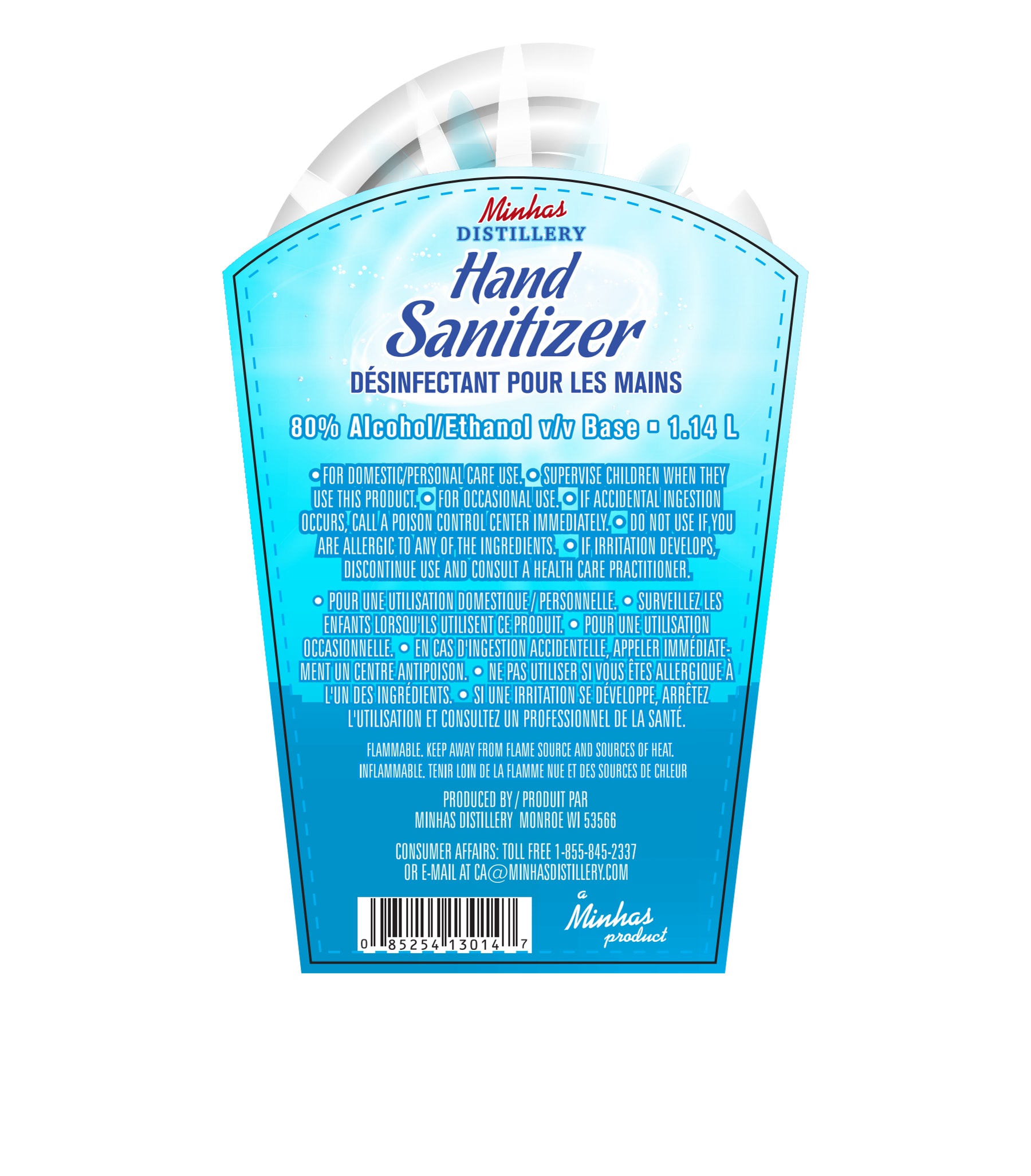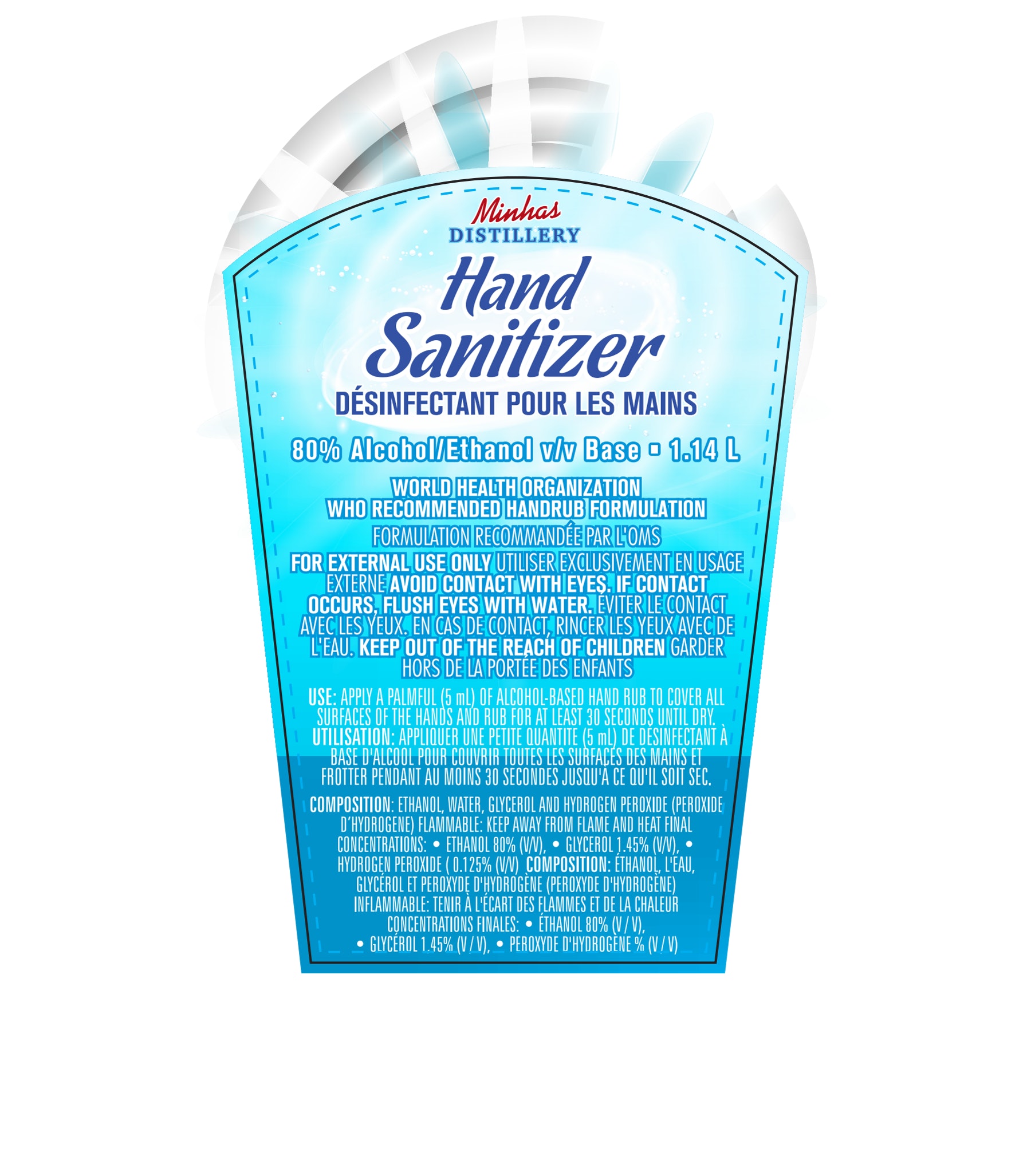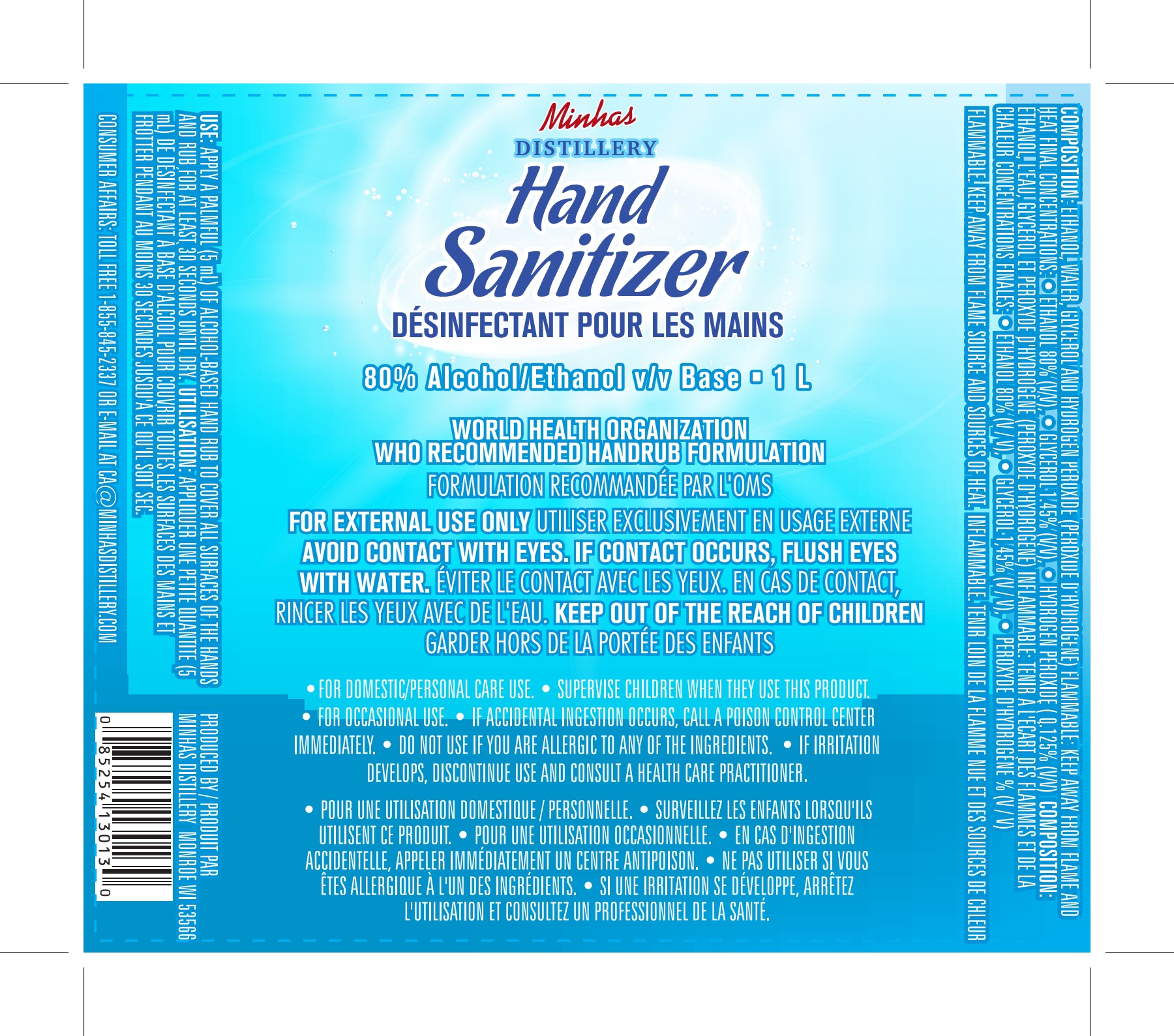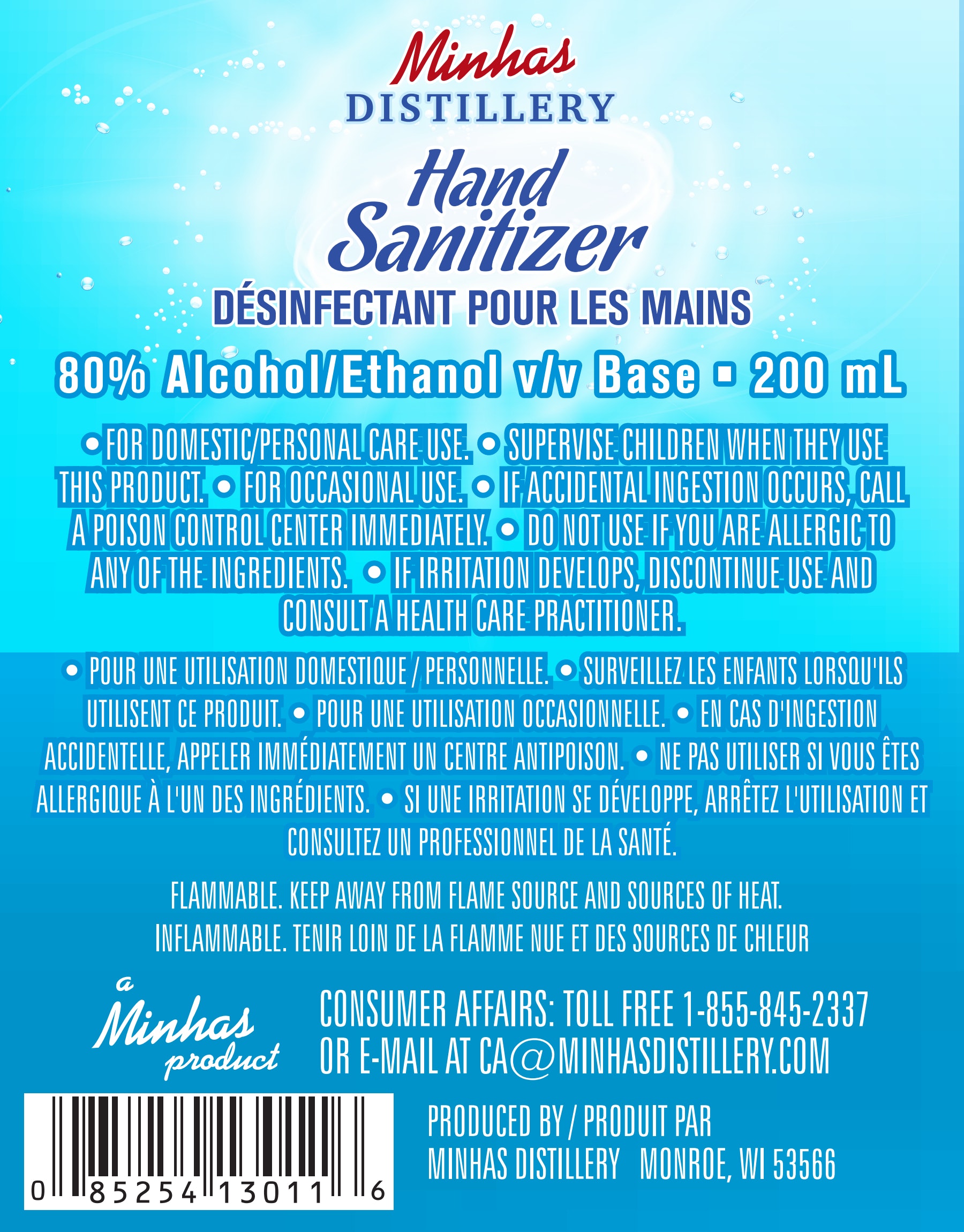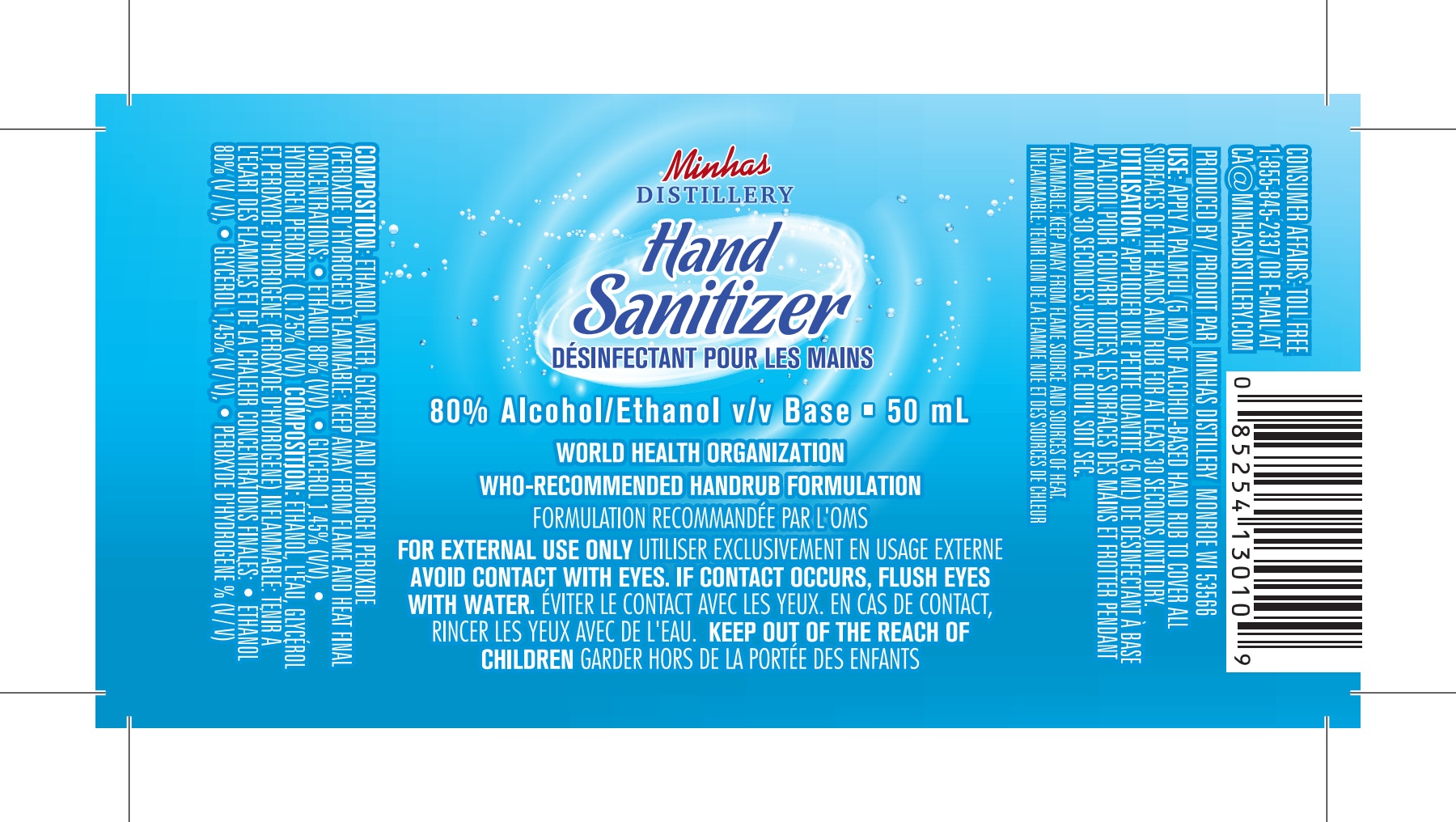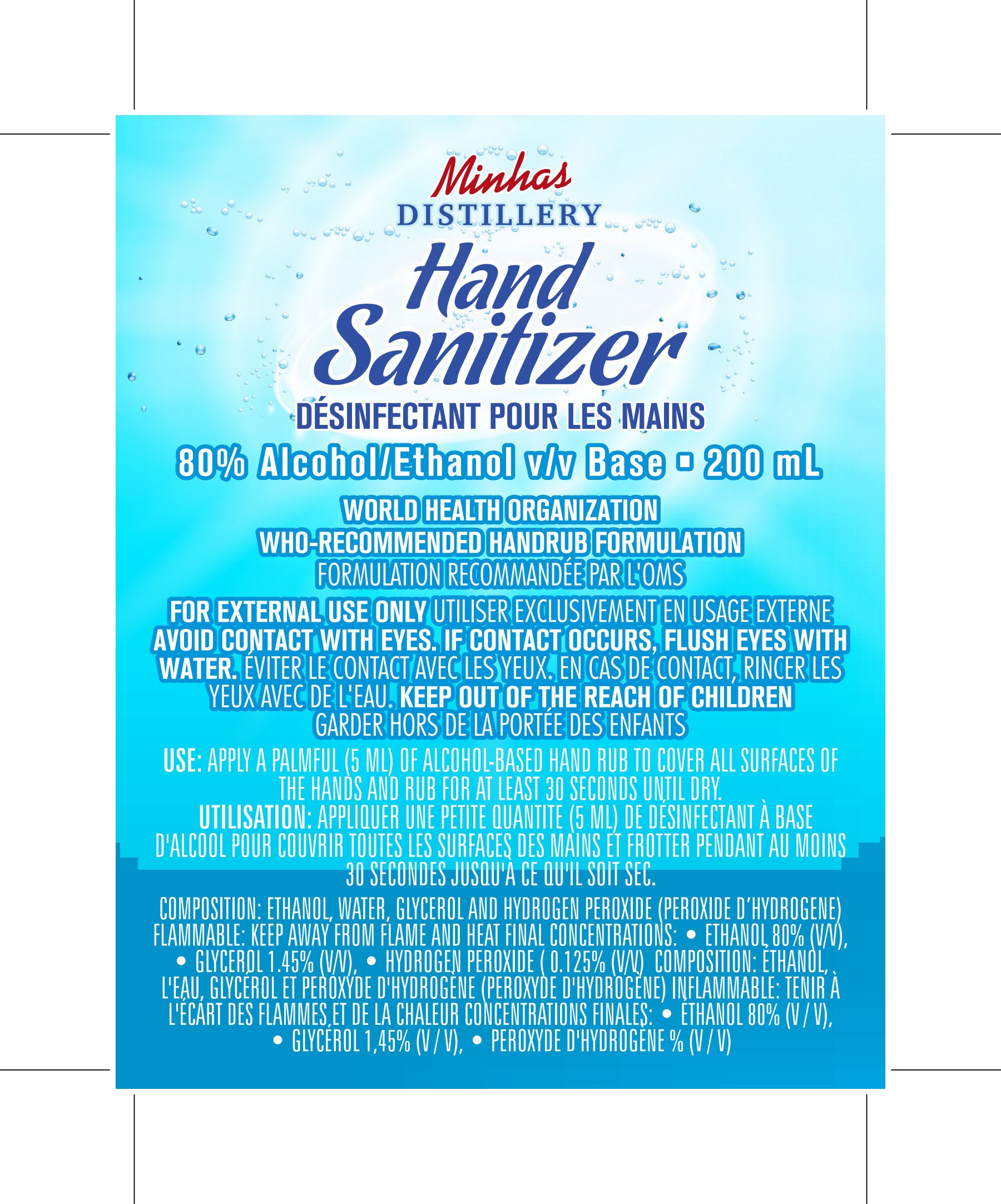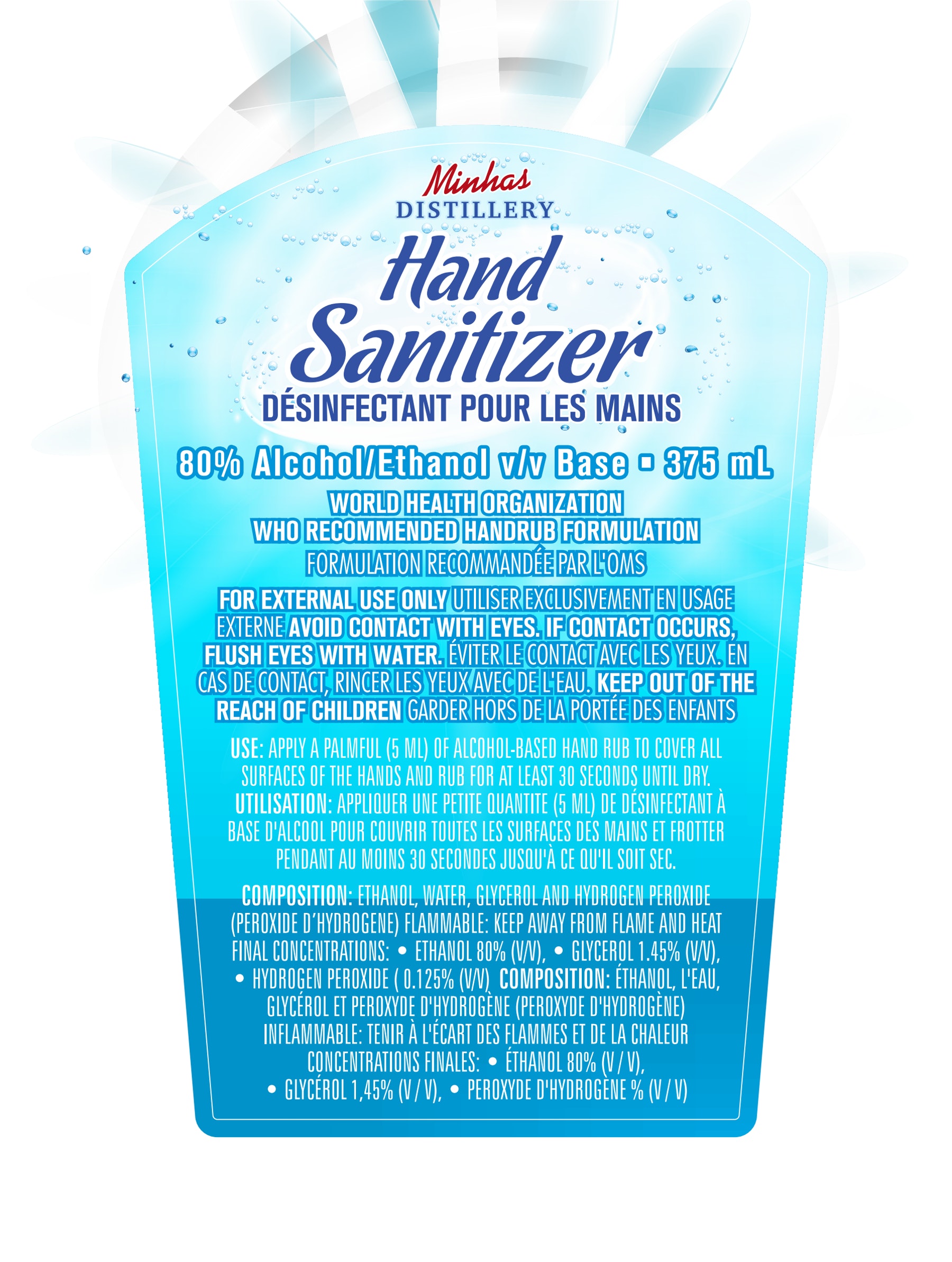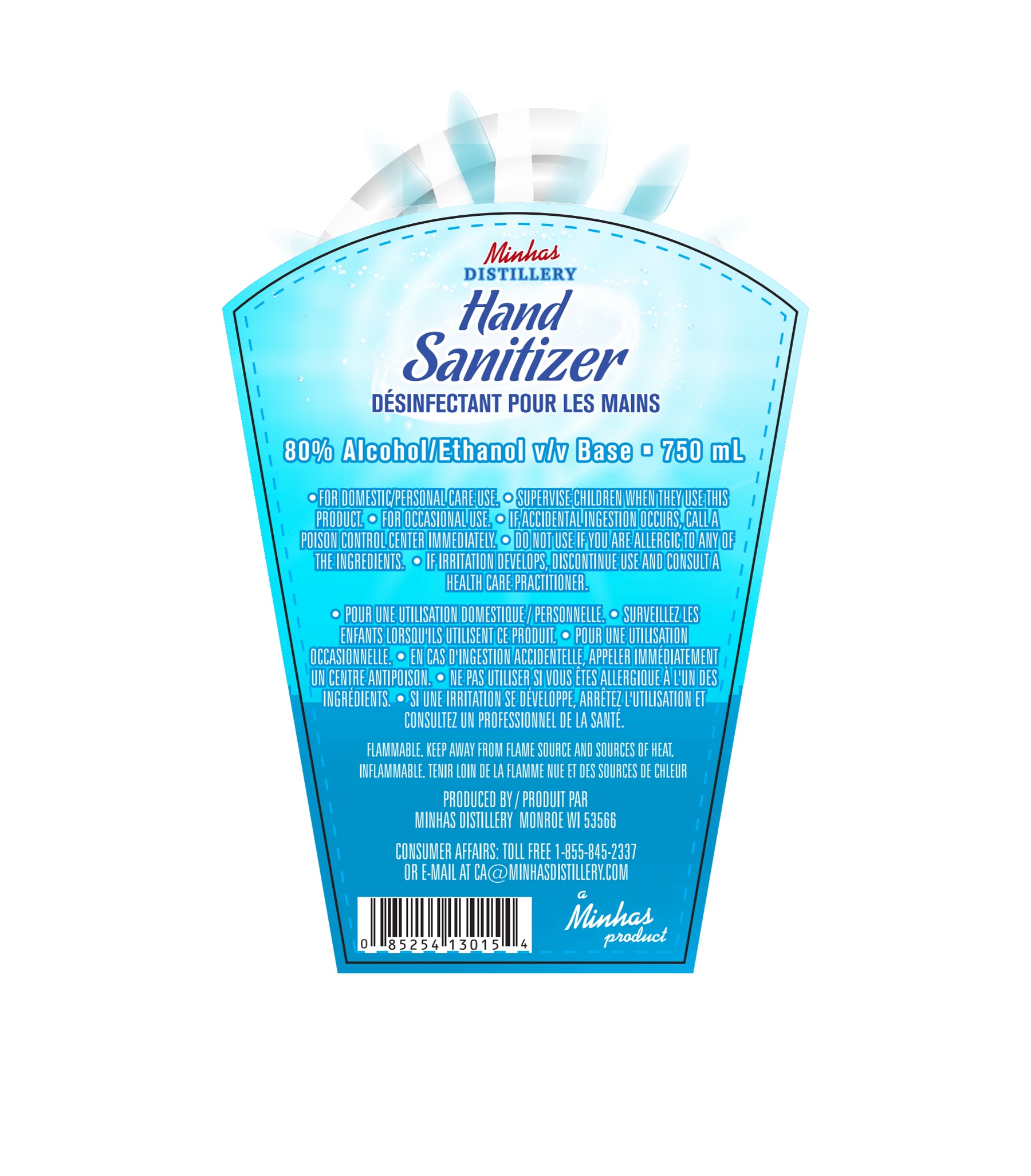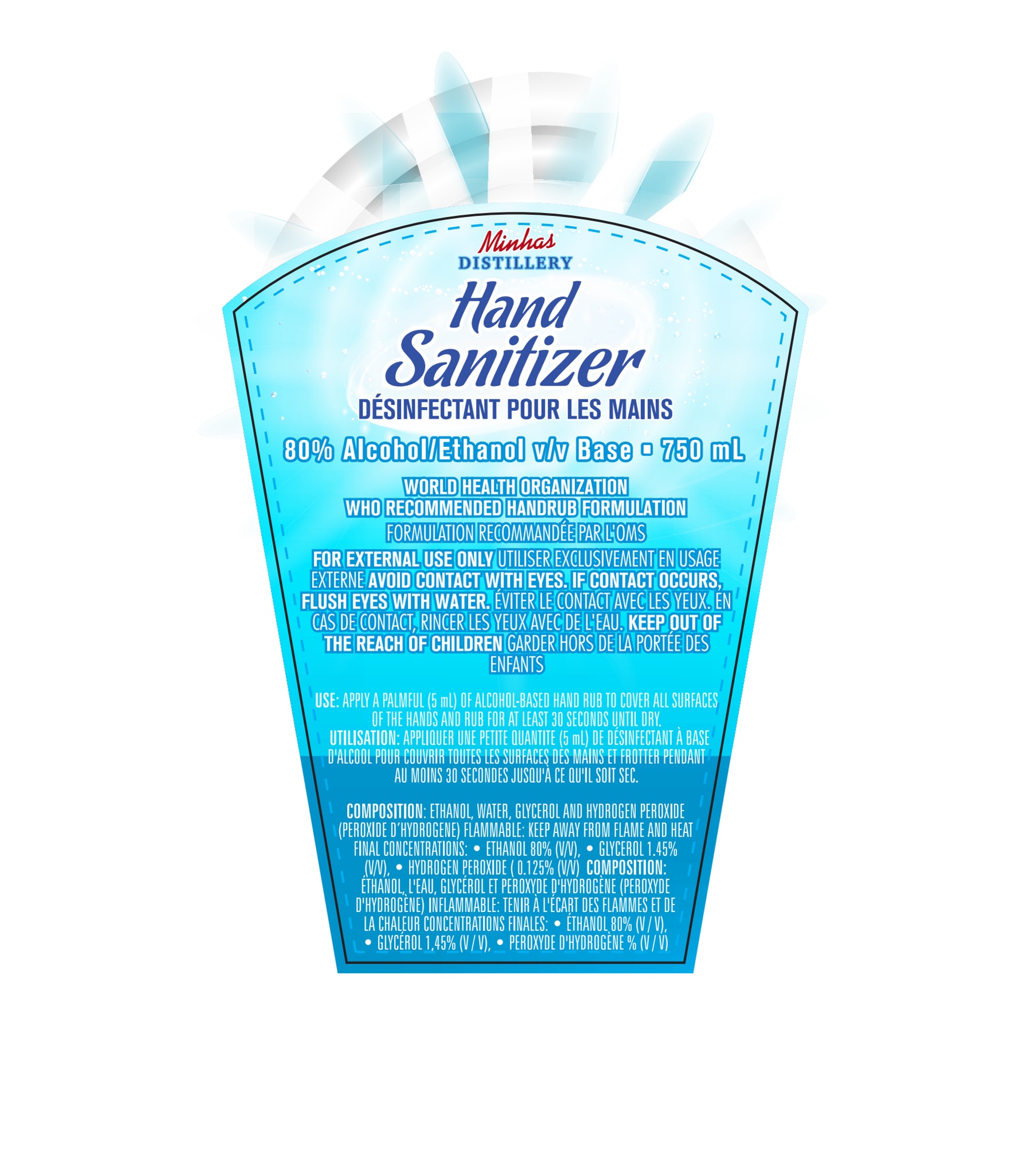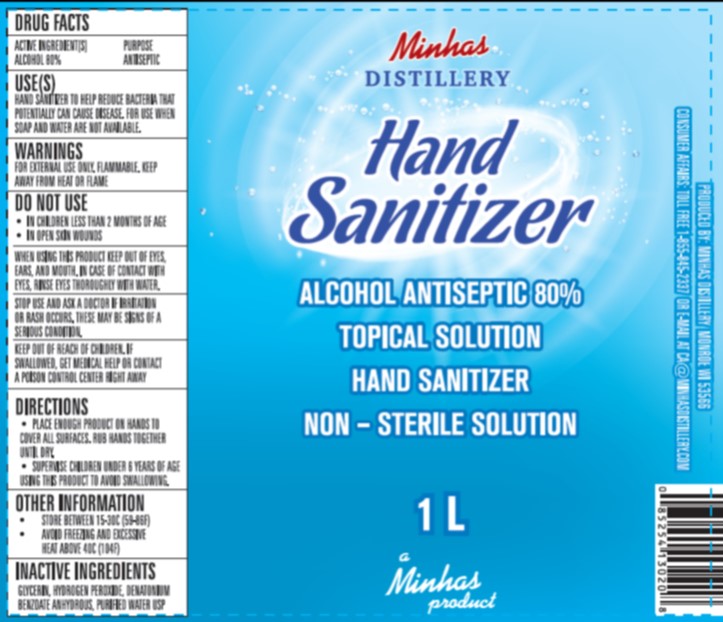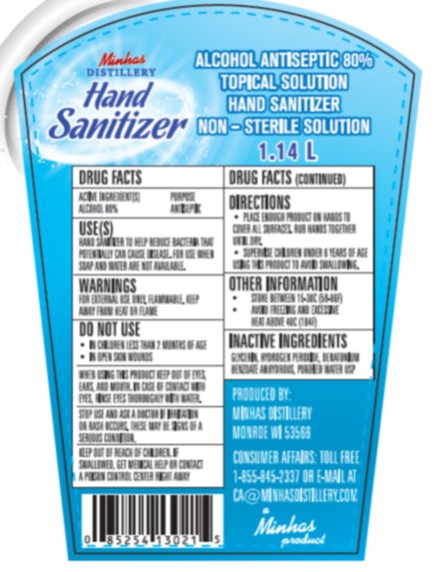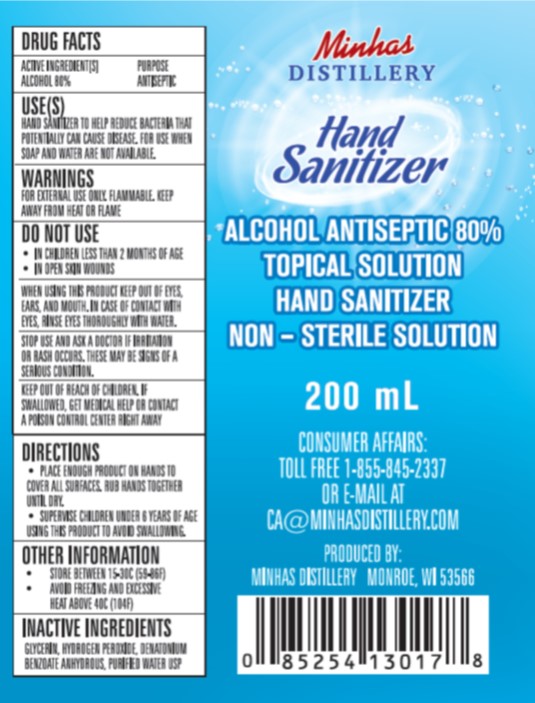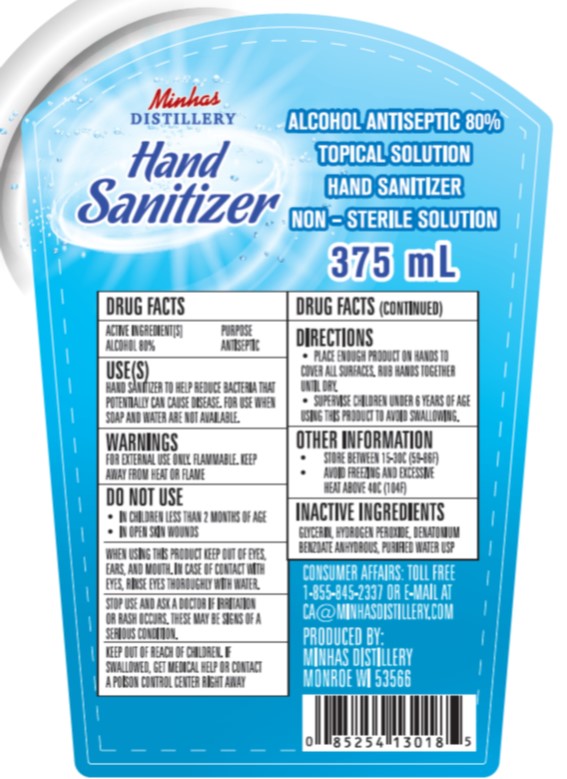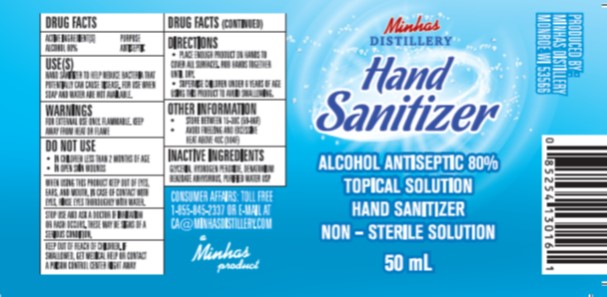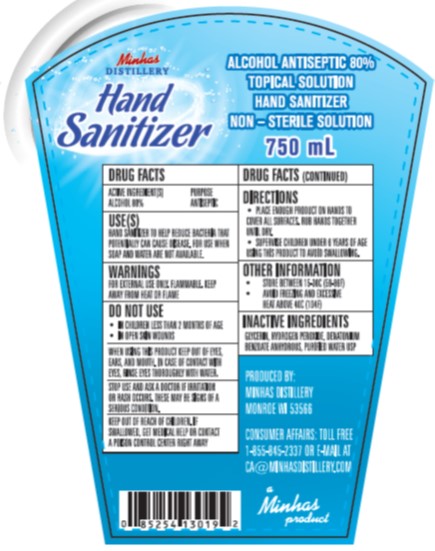 DRUG LABEL: Hand Sanitizer USA
NDC: 74010-3016 | Form: LIQUID
Manufacturer: Global Universal SRL LLC dba Minhas Micro Distillery
Category: otc | Type: HUMAN OTC DRUG LABEL
Date: 20200407

ACTIVE INGREDIENTS: ALCOHOL 80 mL/100 mL
INACTIVE INGREDIENTS: DENATONIUM BENZOATE ANHYDROUS; HYDROGEN PEROXIDE; GLYCERIN; WATER

Minhas Hand Sanitizer